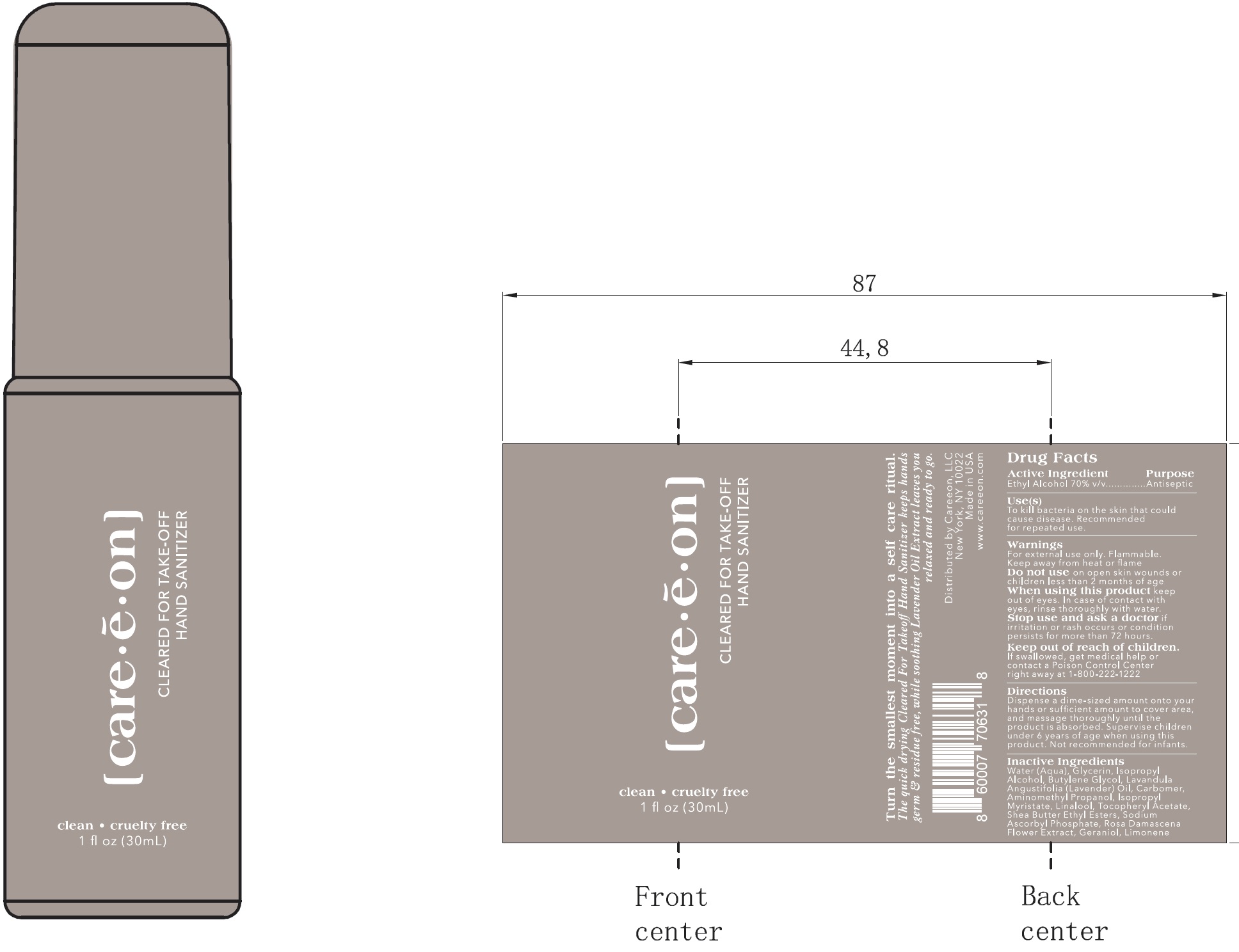 DRUG LABEL: Cleared For Take Off Hand Sanitizer
NDC: 83617-001 | Form: GEL
Manufacturer: Careeon LLC
Category: otc | Type: HUMAN OTC DRUG LABEL
Date: 20231106

ACTIVE INGREDIENTS: ALCOHOL 70 mL/100 mL
INACTIVE INGREDIENTS: WATER; GLYCERIN; ISOPROPYL ALCOHOL; BUTYLENE GLYCOL; LAVENDER OIL; CARBOMER HOMOPOLYMER, UNSPECIFIED TYPE; AMINOMETHYLPROPANOL; ISOPROPYL MYRISTATE; LINALOOL, (+/-)-; .ALPHA.-TOCOPHEROL ACETATE; SHEA BUTTER ETHYL ESTERS; SODIUM ASCORBYL PHOSPHATE; ROSA X DAMASCENA FLOWER; GERANIOL; LIMONENE, (+)-

Cleared For Take Off Hand Sanitizer

Active Ingredient

Ethyl Alcohol 70% v/v

Purpose

Antiseptic

Use(s)

To kill bacteria on the skin that could cause disease. Recommended for repeated use.

Warnings

For external use only. Flammable. Keep away from heat or flame

Do not us

on open skin wounds or children less than 2 months of age

When using this product

keep out of eyes. In case of contact with eyes, rinse thoroughly with water.

Stop us and ask a doctor

if irritation or rash occurs or condition persists for more than 72 hours.

Keep out of reach of children.

If swallowed, get medical help or contact a Poison Control Center right away at 1-800-222-1222

Directions

Dispense a dime-sized amount onto your hands or sufficient amount to cover area, and massage thoroughly until the product is absorbed. Supervise children under 6 years of age when using this product. Not recommended for infants.

Inactive Ingredients

Water (Aqua), Glycerin, Isopropyl Alcohol, Butylene Glycol, Lavandula Angustifolia (Lavender) Oil, Carbomer, Aminomethyl Propanol, Isopropyl Myristate, Linalool, Tocopheryl Acetate, Shea Butter Ethyl Esters, Sodium Ascorbyl Phosphate, Rosa Damascena Flower Extract, Geraniol, Limonene